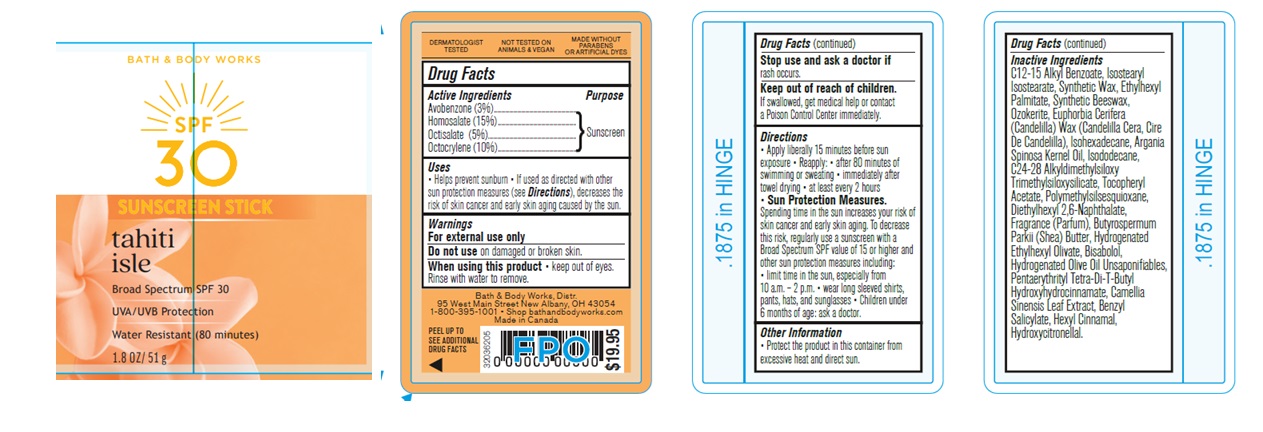 DRUG LABEL: Bath and Body Works SPF
NDC: 62670-6800 | Form: STICK
Manufacturer: Bath & Body Works, Inc.
Category: otc | Type: HUMAN OTC DRUG LABEL
Date: 20250630

ACTIVE INGREDIENTS: OCTOCRYLENE 10 mg/100 mg; AVOBENZONE 3 mg/100 mg; HOMOSALATE 15 mg/100 mg; OCTISALATE 5 mg/100 mg
INACTIVE INGREDIENTS: WATER

SPF Stick Tahiti Isle
(version 2: updated artwork)

Active Ingredients

Avobenzone 3%, Homosalate 15%, Octisalate 5%, Octocrylene 10%

Purpose

Sunscreen

Uses

• helps prevent sunburn • if used as directed with other sun protection measures (see Directions), decreases the risk of skin cancer and early skin aging caused by the sun

Warnings

For external use only

Do not use

on damaged or broken skin

When using this product

keep out of eyes. Rinse with water to remove.

Stop use and ask a doctor

if rash occurs

Keep out of reach of children

If product is swallowed, get medical help or contact a Poison Control Center immediately.

Directions

• apply liberally 15 minutes before sun exposure • reapply: • after 80 minutes of swimming or sweating • immediately after towel drying • at least every 2 hours • Sun Protection Measures. Spending time in the sun increases your risk of skin cancer and early skin aging. To decrease this risk, regularly use a sunscreen with a broad spectrum SPF of 15 or higher and other sun protection measures including: • limit time in the sun, especially from 10 a.m. - 2 p.m. • wear long-sleeved shirts, pants, hats, and sunglasses • children under 6 months: Ask a doctor

Inactive ingredients

C12-15 Alkyl Benzoate, Isostearyl Isostearate, Synthetic Wax, Ethylhexyl Palmitate, Synthetic Beeswax, Ozokerite, Euphorbia Cerifera (Candelilla) Wax (Candelilla Cera, Cire de candelilla), Isohexadecane, Argania Spinosa Kernel Oil, Isododecane, C24-28 Alkyldimethylsiloxy Trimethylsiloxysilicate, Tocopheryl Acetate, Polymethylsilsesquioxane, Diethylhexyl 2,6-Naphthalate, Fragrance (Parfum), Butyrospermum Parkii (Shea) Butter, Hydrogenated Ethylhexyl Olivate, Bisabolol, Hydrogenated Olive Oil Unsaponifiables, Pentaerythrityl Tetra-di-t-butyl Hydroxyhydrocinnamate, Camellia Sinensis Leaf Extract, Benzyl Salicylate, Hexyl Cinnamal, Hydroxycitronellal.

Other information

• protect this product from excessive heat and direct sun

Bath & Body Works, Distr.

95 West Main Street New Albany, OH 43054

1-800-395-1001

shop bathandbodyworks.com